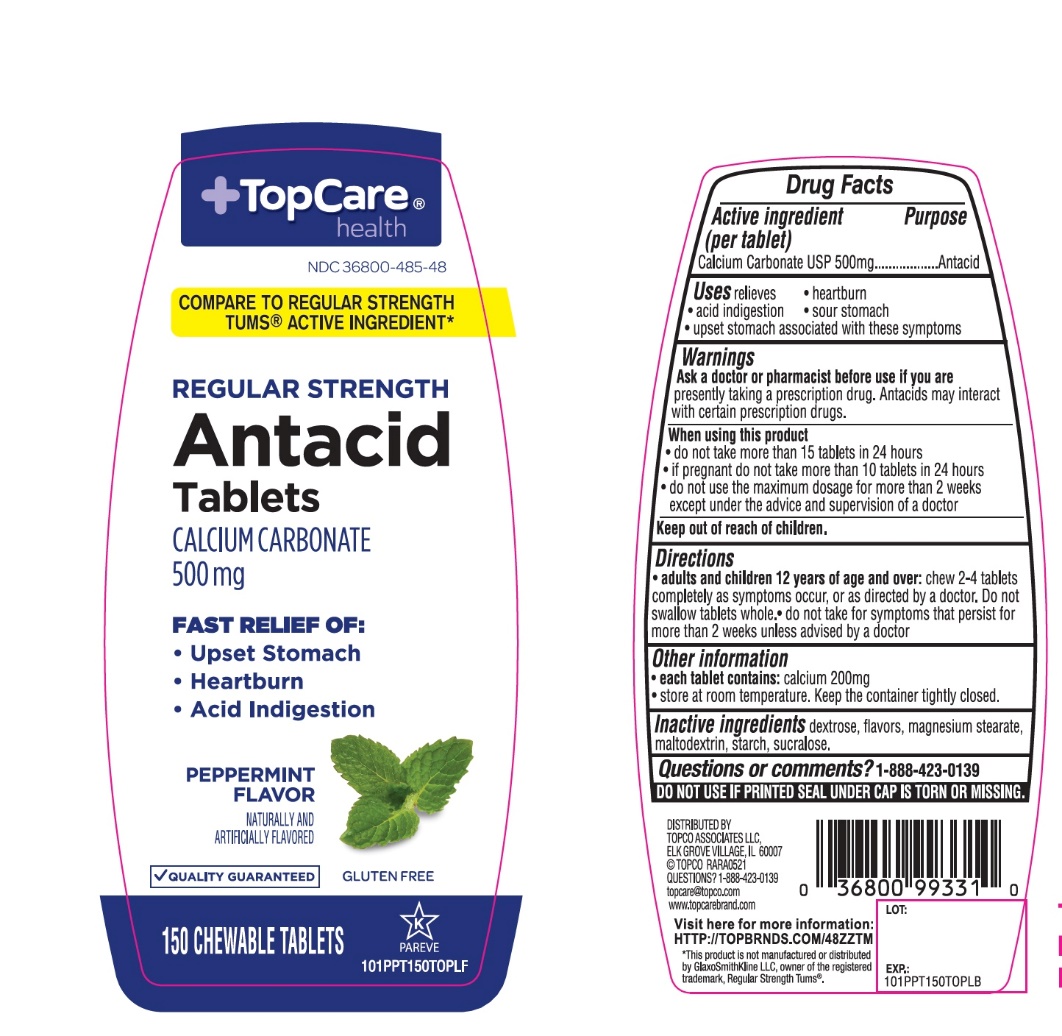 DRUG LABEL: Topcare Antacid Calcium

NDC: 36800-485 | Form: TABLET, CHEWABLE
Manufacturer: Topco Associates LLC
Category: otc | Type: HUMAN OTC DRUG LABEL
Date: 20251108

ACTIVE INGREDIENTS: CALCIUM CARBONATE 500 mg/1 1
INACTIVE INGREDIENTS: DEXTROSE, UNSPECIFIED FORM; MAGNESIUM STEARATE; MALTODEXTRIN; STARCH, CORN; SUCRALOSE

Topco Associates LLC. Antacid Calcium Drug Facts

Active ingredient (per tablet)

Calcium Carbonate USP 500mg

Purpose

Antacid

Uses

relieves

- heartburn
- acid indigestion
- sour stomach
- upset stomach associated with these symptoms

Warnings

Ask a doctor or pharmacist before use if you are

presently taking a prescription drug. Antacids may interact with certain prescription drugs.

When using this product

- do not take more than 15 tablets in 24 hours
- if pregnant do not take more than 10 tablets in 24 hours
- do not use the maximum dosage for more than 2 weeks except under the advice and supervision of a doctor

Directions

- adults and children 12 years of age and older:chew 2-4 tablets as symptoms occur, or as directed by a doctor
- do not take for symptoms that persist for more than 2 weeks unless advised by a doctor

Other information

- each tablet contains: elemental calcium 200mg
- store at room temperature. Keep the container tightly closed.

Inactive ingredients

dextrose, flavor, magnesium stearate, maltodextrin, starch, sucralose.

Questions or comments?

1-888-423-0139

Safety sealed:Do not use if printed seal under cap is torn or missing.

Principal Display Panel

+TopCare®health™

NDC#36800-485-48

COMPARE TO REGULAR STRENGTH TUMS® ACTIVE INGREDIENT*

REGULAR STRENGTH

Antacid Tablets

CALCIUM CARBONATE 500mg

OUR PHARMACISTS RECOMMEND

FAST RELIEF OF:

- Upset Stomach
- Heartburn
- Acid Indigestion

PEPPERMINT FLAVOR

- QUALITY GUARANTEED

GLUTEN FREE

150 CHEWABLE TABLETS

K PAREVE

DISTRIBUTED BY

TOPCO ASSOCIATES LLC

ELK GROVE VILLAGE, IL 60007

©TOPCO RARA0918

QUESTIONS? 1-888-423-0139

topcare@topco.comwww.topcarebrand.com

Visit here for more information: http://topbrnds.com/48ZSOL

*This product is not manufactured or distributed by GlaxoSmithKline LLC, owner of the registered trademark, Regular Strength Tums®.